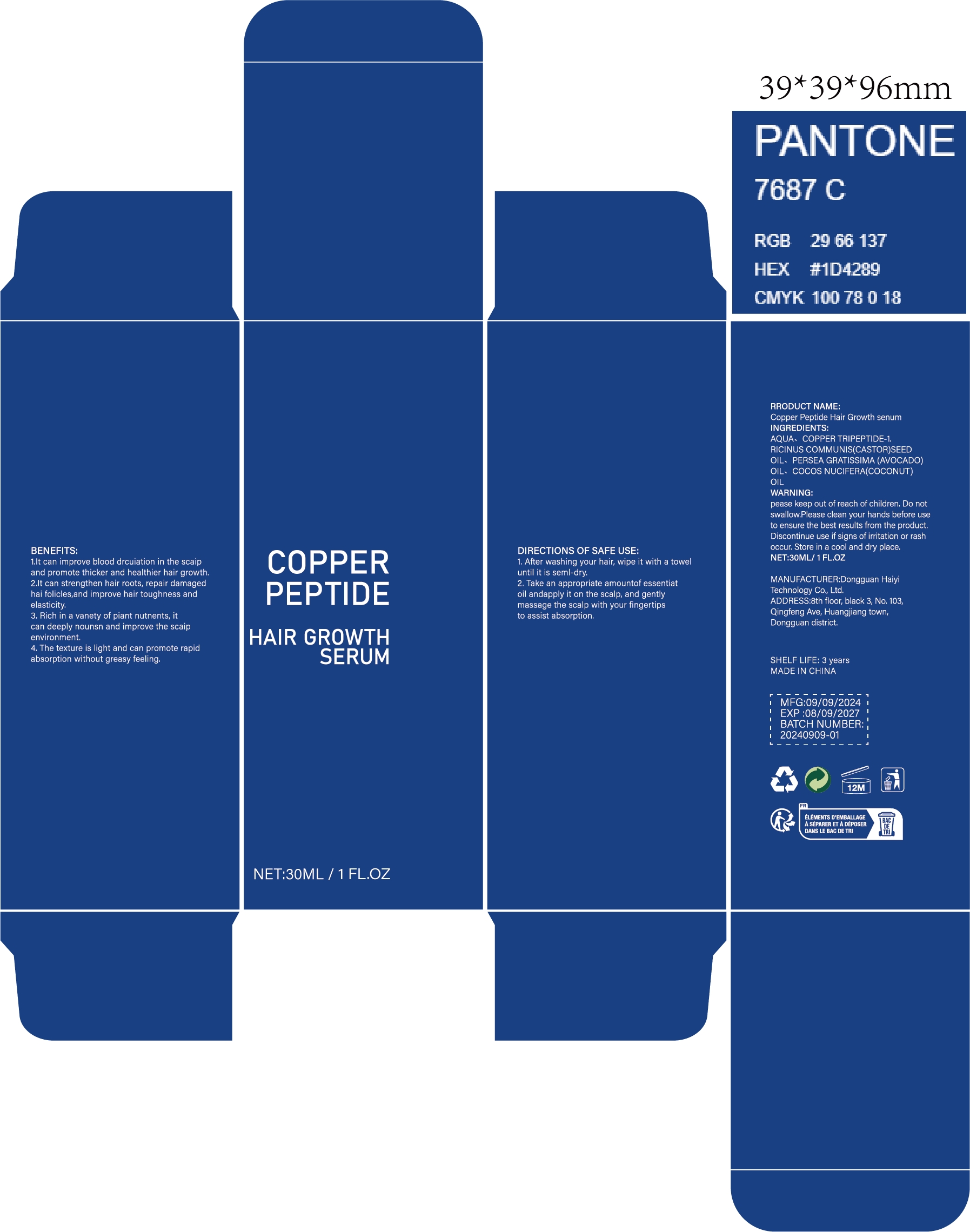 DRUG LABEL: Copper Peptide Hair Growth senum
NDC: 84732-028 | Form: LIQUID
Manufacturer: Dongguan Haiyi Technology Co.,Ltd.
Category: otc | Type: HUMAN OTC DRUG LABEL
Date: 20240929

ACTIVE INGREDIENTS: PREZATIDE COPPER 1 mg/30 mL
INACTIVE INGREDIENTS: COCONUT OIL; CASTOR OIL; WATER; AVOCADO OIL

Active ingredient

COPPER TRIPEPTIDE-1

Inactive ingredient

AQUA

RICINUS COMMUNIS (CASTOR) SEED OIL

PERSEA GRATISSIMA (AVOCADO)OIL

COCOS NUCIFERA (COCONUT) OIL

Purpose section

1.lt can improve blood drcuiation in the scaipand promote thicker and healthier hair growth,

2.lt can strengthen hair roots, repair damagedhai folicles,and improve hair toughness andelasticity.

3. Rich in a vanety of piant nutnents, itcan deeply nounsn and improve the scaipenvironment.

4. The texture is light and can promote rapidabsorption without greasy feeling.

Warning

pease keep out of reach of children, Do not swallow,Please clean your hands before use to ensure the best results from the product.Discontinue use if signs of irritation or rash occur, Store in a cool and dry place.

stop use

This product may cause allergic reactions in asmall number of people.
lf youexperience any discomfort,please stop using it immediately.

not use

Not suitable for use by children, pregnantor breast feeding people.

OUT OF CHILDREN

KEEP THE PRODUCT OUT OF REACH OF CHILDREN to

HOW TO USE

1. After washing your hair, wipe it with a toweluntil it is seml-dry.

2. Take an appropriate amountof essentiatoil andapply it on the scalp, and gentlymassage the scalp with your fingertipsto assist absorption.

Dosage

take an appropriateamount,Use 2-3 times a week